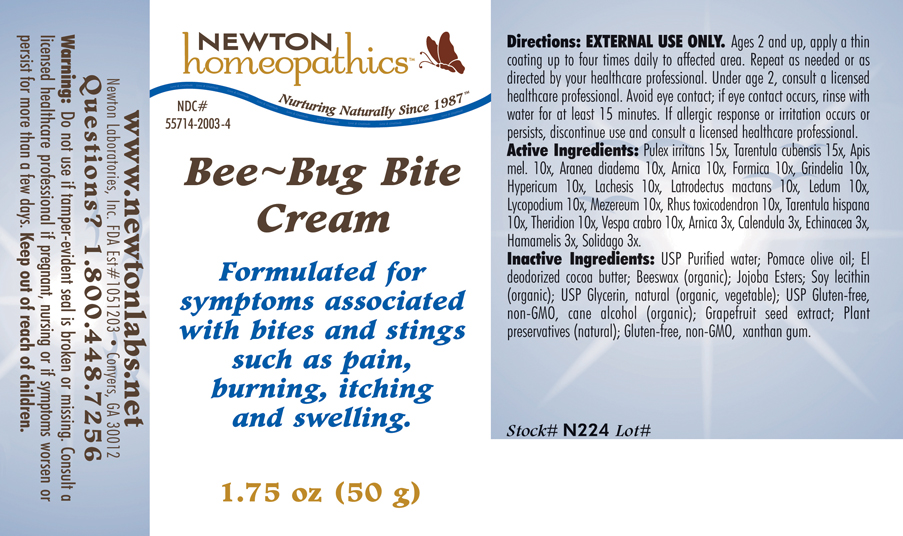 DRUG LABEL: Bee - Bug Bite 
NDC: 55714-2003 | Form: CREAM
Manufacturer: Newton Laboratories, Inc.
Category: homeopathic | Type: HUMAN OTC DRUG LABEL
Date: 20130801

ACTIVE INGREDIENTS: Pulex Irritans 15 [hp_X]/1 g; Citharacanthus Spinicrus 15 [hp_X]/1 g; Apis Mellifera 10 [hp_X]/1 g; Araneus Diadematus 10 [hp_X]/1 g; Arnica Montana 10 [hp_X]/1 g; Formica Rufa 10 [hp_X]/1 g; Grindelia Hirsutula Flowering Top 10 [hp_X]/1 g; Hypericum Perforatum 10 [hp_X]/1 g; Lachesis Muta Venom 10 [hp_X]/1 g; Latrodectus Mactans 10 [hp_X]/1 g; Ledum Palustre Twig 10 [hp_X]/1 g; Lycopodium Clavatum Spore 10 [hp_X]/1 g; Daphne Mezereum Bark 10 [hp_X]/1 g; Toxicodendron Pubescens Leaf 10 [hp_X]/1 g; Lycosa Tarantula 10 [hp_X]/1 g; Theridion Curassavicum 10 [hp_X]/1 g; Vespa Crabro 10 [hp_X]/1 g; Calendula Officinalis Flowering Top 3 [hp_X]/1 g; Echinacea, Unspecified 3 [hp_X]/1 g; Hamamelis Virginiana Root Bark/stem Bark 3 [hp_X]/1 g; Solidago Virgaurea Flowering Top 3 [hp_X]/1 g
INACTIVE INGREDIENTS: Water; Olive Oil; Cocoa Butter; Royal Jelly; Jojoba Oil; Lecithin, Soybean; Glycerin; Alcohol; Citrus Paradisi Seed; Xanthan Gum; Lonicera Japonica Flower

Bee - Bug Bite Cream

INDICATIONS & USAGE SECTION

Bee - Bug Bite Cream: Formulated for symptoms associated with bites and stings such as pain, burning, itching and swelling.

DOSAGE & ADMINISTRATION SECTION

Directions: EXTERNAL USE ONLY: Ages 2 and up, apply a thin coating up to four times daily to affected area. Repeat as needed or as directed by your healthcare professional. Under age 2, consult a licensed healthcare professional. Avoid eye contact; if eye contact occurs, rinse with water for at least 15 minutes. If allergic response or irritation occurs or persists, discontinue use and consult a licensed healthcare professional.

OTC - ACTIVE INGREDIENT SECTION

Pulex irritans 15x, Tarentula cubensis 15x, Apis mel. 10x, Aranea diadema 10x, Arnica 10x, Formica 10x, Grindelia 10x, Hypericum 10x, Lachesis 10x, Latrodectus mactans 10x, Ledum 10x, Lycopodium 10x, Mezereum 10x, Rhus toxicodendron 10x, Tarentula hispana 10x, Theridion 10x, Vespa crabro 10x, Arnica 3x, Calendula 3x, Echinacea 3x, Hamamelis 3x, Solidago 3x.

OTC - PURPOSE SECTION

Formulated for symptoms associated with bites and stings such as pain, burning, itching and swelling.

INACTIVE INGREDIENT SECTION

USP Purified Water, Pomace Olive Oil, El Deodorized Cocoa Butter, Beeswax (organic), Jojoba Esters, Soy Lecithin (organic), USP Glycerin, natural (organic, vegetable), USP Gluten-free, non-GMO Cane Alcohol (organic), Grapefruit Seed Extract, Plant preservatives (natural), Gluten-free, non-GMO Xanthan Gum.

QUESTIONS SECTION

www.newtonlabs.net Newton Laboratories, Inc. FDA Est # 1051203 - Conyers, GA 30012 Questions? 1.800.448.7256

WARNINGS SECTION

Warning: Do not use if tamper - evident seal is broken or missing. Consult a licensed healthcare professional if pregnant, nursing or if symptoms worsen or persist for more than a few days. Keep out of reach of children.

OTC - PREGNANCY OR BREAST FEEDING SECTION

Consult a licensed healthcare professional if pregnant, nursing or if symptoms worsen or persist for more than a few days.

OTC - KEEP OUT OF REACH OF CHILDREN SECTION

Keep out of reach of children.